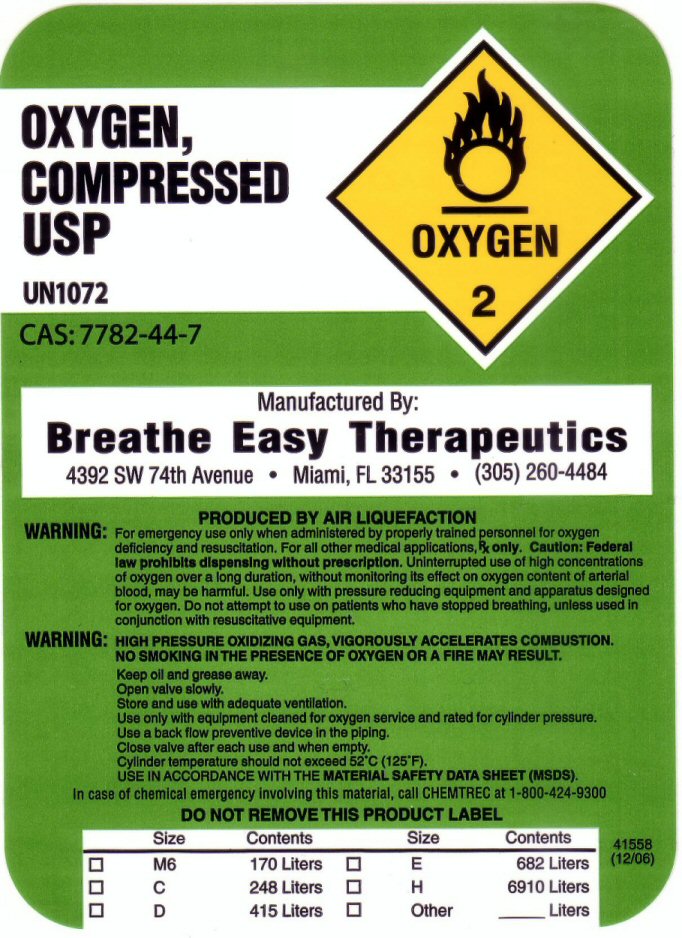 DRUG LABEL: OXYGEN
NDC: 65856-216 | Form: GAS
Manufacturer: Breathe Easy Therapeutics, Inc
Category: prescription | Type: HUMAN PRESCRIPTION DRUG LABEL
Date: 20100101

ACTIVE INGREDIENTS: OXYGEN 99 L/100 L

OXYGEN COMPRESSED LABEL

OXYGEN COMPRESSED USP UN 1072 OXYGEN-2 CAS:7782-44-7

PRODUCED BY AIR LIQUEFACTION. WARNING: FOR EMERGENCY USE ONLY WHEN ADMINISTERED BY PROPERLY TRAINED PERSONNEL FOR OXYGEN DEFICIENCY AND RESUSCITATION. FOR ALL OTHER MEDICAL APPLICATIONS Rx ONLY. CAUTION: FEDERAL LAW PROHIBITS DISPENSING WITHOUT A PRESCRIPTION. UNINTERRUPTED USE OF HIGH CONCENTRATIONS OF OXYGEN OVER A LONG DURATION WITHOUT MONITORING ITS EFFECT ON OXYGEN CONTENT OF ARTERIAL BLOOD MAY BE HARMFUL. USE ONLY WITH PRESSURE REDUCING EQUIPMENT AND APPARATUS DESIGNED FOR OXYGEN. DO NOT ATTEMPT TO USE ON PATIENTS WHO HAVE STOPPED BREATHING, UNLESS USED IN CONJUNCTION WITH RESUSCITATIVE EQUIPMENT. WARNING: HIGH PRESSURE OXIDIZING GAS, VIGOROUSLY ACCELERATES COMBUSTION NO SMOKING IN THE PRESENCE OF OXYGEN OR A FIRE MAY RESULT. KEEP OIL AND GREASE AWAY. OPEN VALVE SLOWLY. STORE AND USE WITH ADEQUATE VENTILATION. USE ONLY WITH EQUIPMENT CLEANED FOR OXYGEN SERVICE AND RATED FOR CYLINDER PRESSURE. USE A BACK FLOW PREVENTATIVE DEVICE IN THE PIPING. CLOSE VALVE AFTER EACH USE AND WHEN EMPTY. CYLINDER TEMPERATURE SHOULD NOT EXCEED 52 C (125 F) USE IN ACCORDANCE WITH THE MATERIAL SAFETY DATA SHEET (MSDS) IN CASE OF CHEMICAL EMERGENCY INVOLVING THIS MATERIAL CALL CHEMTREC AT 1-800-424-9300 DO NOT REMOVE THIS PRODUCT LABEL

SIZE CONTENTS

M6 170 LITERS

C 248 LITERS

D 415 LITERS

E 682 LITERS

H 6910 LITERS

OTHER